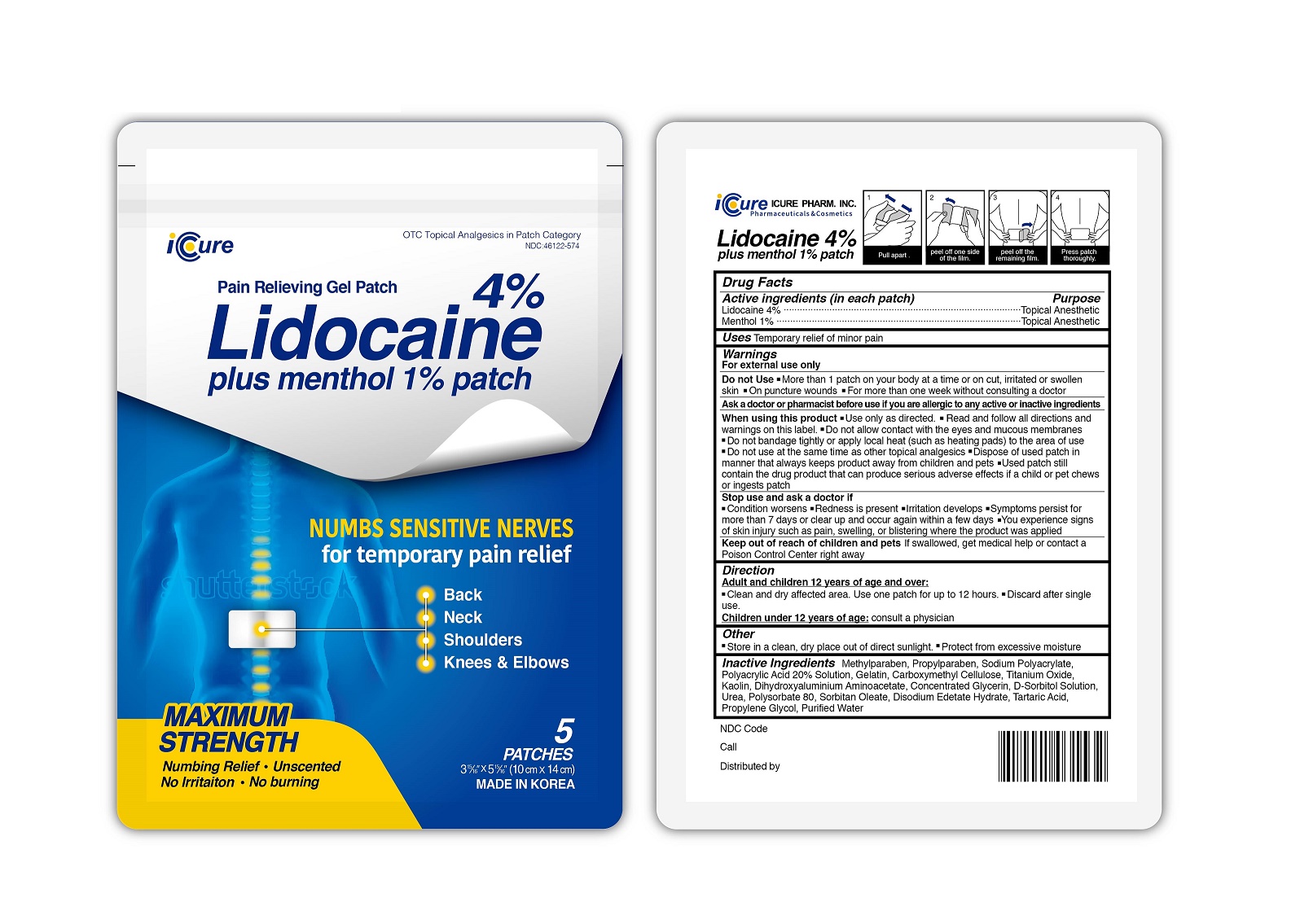 DRUG LABEL: Lidocaine 4% plus Menthol 1%
NDC: 73279-0001 | Form: PATCH
Manufacturer: Icure Pharmaceutical Inc, Wanju Factory
Category: otc | Type: HUMAN OTC DRUG LABEL
Date: 20190903

ACTIVE INGREDIENTS: MENTHOL 1 g/100 g; LIDOCAINE 4 g/100 g
INACTIVE INGREDIENTS: METHYLPARABEN; PROPYLPARABEN

Drug Facts

ACTIVE INGREDIENT

lidocaine, menthol

INACTIVE INGREDIENT

Methylparaben, Propylparaben, Sodium Polyacrylate, Polyacrylic Acid 20% Solution, Gelatin, Carboxymethyl Cellulose, Titanium Oxide, Kaolin, Dihydroxyaluminium Aminoacetate, Concentrated Glycerin, D-Sorbitol Solution, Urea, Polysorbate 80, Sorbitan Oleate, Disodium Edetate Hydrate, Tartaric Acid, Propylene Glycol, Purified Water

PURPOSE

Temporary relief of minor pain

keep out of reach of the children

INDICATIONS AND USAGE

Use only as directed. Read and follow all directions and warnings on this label.
Do not allow contact with the eyes and mucous membranes
Do not bandage tightly or apply local heat (such as heating pads) to the area of use
Do not use at the same time as other topical analgesics
Dispose of used patch in manner that always keeps product away from children and pets
Used patch still contain the drug product that can produce serious adverse effects if a child or pet chews or ingests patch

- Warnings
For external use only.
Ask a doctor or pharmacist before use if you are allergic to any active or inactive ingredients.

- Do not Use
More than 1 patch on your body at a time or on cut, irritated or swollen skin
On puncture wounds
For more than one week without consulting a doctor

DOSAGE AND ADMINISTRATION

for external use only